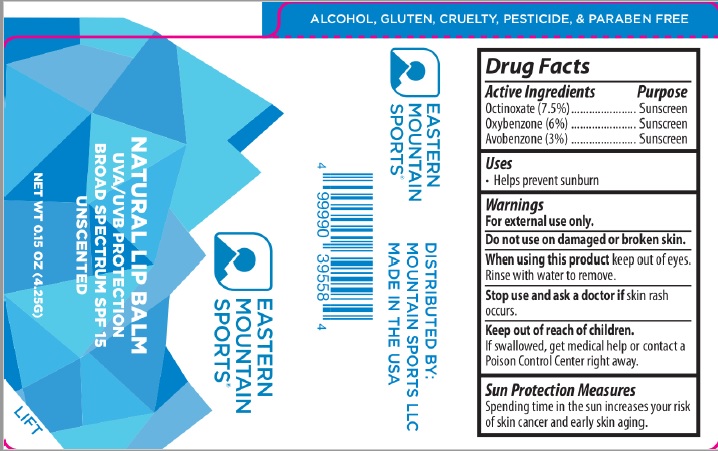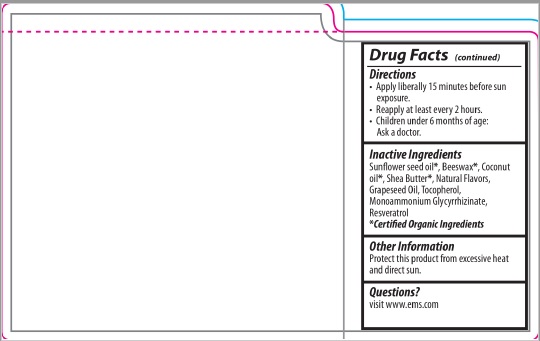 DRUG LABEL: LIP BALM
NDC: 62932-186 | Form: STICK
Manufacturer: Private Label Select Ltd CO
Category: otc | Type: HUMAN OTC DRUG LABEL
Date: 20181130

ACTIVE INGREDIENTS: OXYBENZONE 6 g/100 g; AVOBENZONE 3 g/100 g; OCTINOXATE 7.5 g/100 g
INACTIVE INGREDIENTS: TANGERINE PEEL; AMMONIUM GLYCYRRHIZATE; RESVERATROL; GRAPE SEED OIL; TOCOPHEROL; YELLOW WAX; HELIANTHUS ANNUUS SEED WAX; ORANGE OIL

EMS Natural Lip Balm SPF15